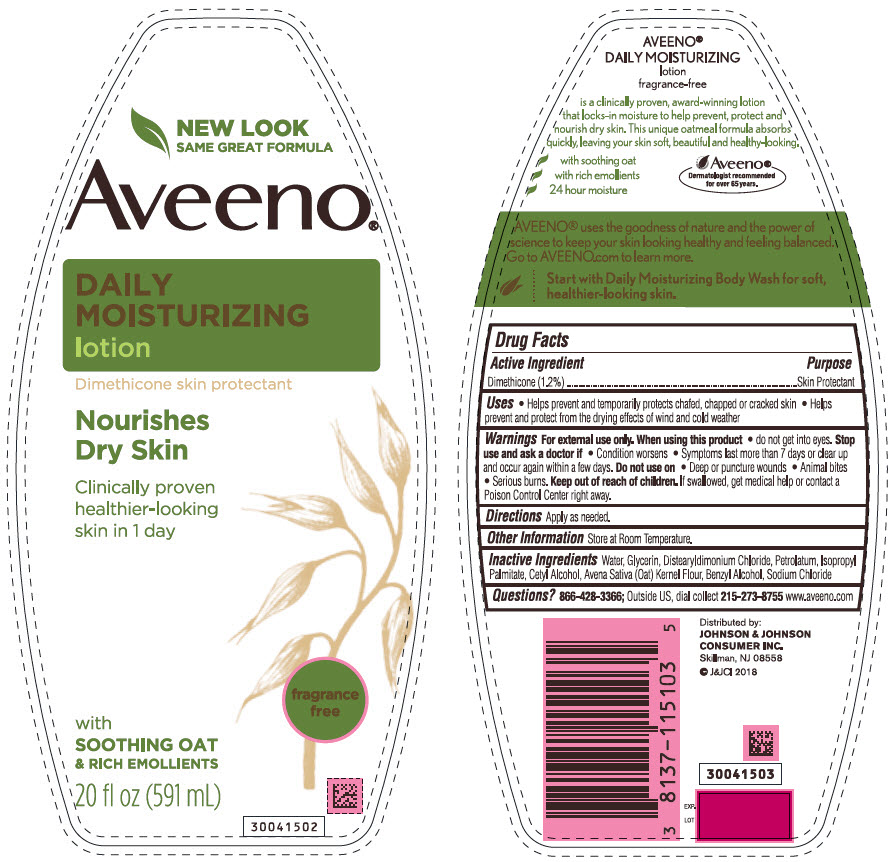 DRUG LABEL: Aveeno DAILY MOISTURIZING
NDC: 69968-0454 | Form: LOTION
Manufacturer: Kenvue Brands LLC
Category: otc | Type: HUMAN OTC DRUG LABEL
Date: 20250716

ACTIVE INGREDIENTS: DIMETHICONE 12 mg/1 mL
INACTIVE INGREDIENTS: WATER; GLYCERIN; DISTEARYLDIMONIUM CHLORIDE; PETROLATUM; ISOPROPYL PALMITATE; CETYL ALCOHOL; OAT; BENZYL ALCOHOL; SODIUM CHLORIDE

Aveeno® daily moisturizing lotion

Drug Facts

Active ingredient

Dimethicone (1.2%)

Purpose

Skin protectant

Uses

- Helps prevent and temporarily protects chafed, chapped or cracked skin
- Helps prevent and protect from the drying effects of wind and cold weather

Warnings

For external use only.

When using this product

- do not get into eyes.

Stop use and ask a doctor if

- Condition worsens
- Symptoms last more than 7 days or clear up and occur again within a few days.

Do not use on

- Deep or puncture wounds
- Animal bites
- Serious burns.

Keep out of reach of children. If swallowed, get medical help or contact a Poison Control Center immediately.

Directions

Apply as needed.

Other information

Store at Room Temperature

Inactive ingredients

Water, Glycerin, Distearyldimonium Chloride, Petrolatum, Isopropyl Palmitate, Cetyl Alcohol, Avena Sativa (Oat) Kernel Flour, Benzyl Alcohol, Sodium Chloride

Questions?

866-428-3366; outside US, dial collect 215-273-8755 www.aveeno.com

Distributed by:
JOHNSON & JOHNSON
CONSUMER INC.
Skillman, NJ 08558

PRINCIPAL DISPLAY PANEL - 591 mL Bottle Label

NEW LOOK
SAME GREAT FORMULA

Aveeno ®
DAILY
MOISTURIZING
Lotion
Dimethicone skin protectant
Nourishes
Dry Skin
Clinically proven
healthier-looking
skin in 1 day

fragrance
free

with
SOOTHING OAT
& RICH EMOLLIENTS
20 fl oz (591 mL)